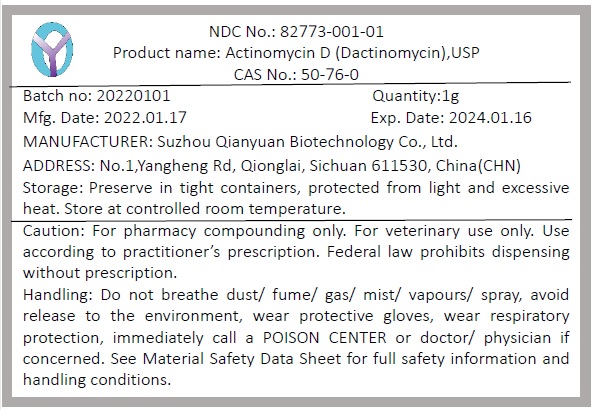 DRUG LABEL: Actinomycin D (Dactinomycin)
NDC: 82773-001 | Form: POWDER
Manufacturer: Suzhou Qianyuan Biotechnology Co., Ltd.
Category: other | Type: BULK INGREDIENT - ANIMAL DRUG
Date: 20220623

ACTIVE INGREDIENTS: DACTINOMYCIN 1 g/1 g

Actinomycin D (Dactinomycin)